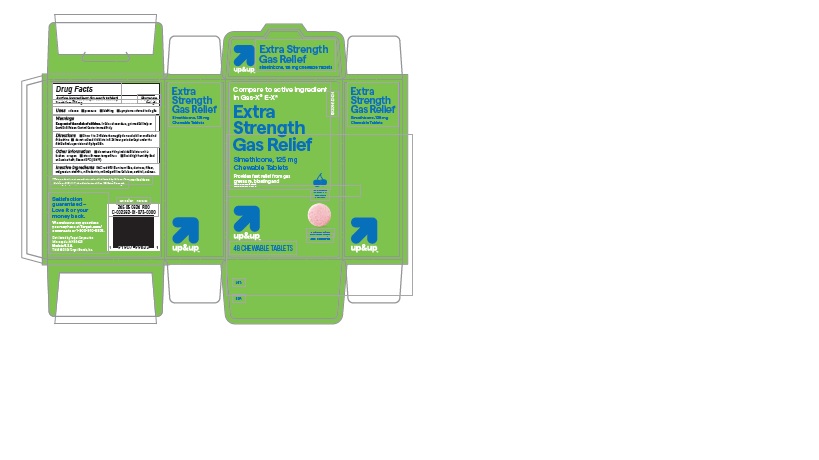 DRUG LABEL: up and up Extra Strength Gas Relief Cherry 134
NDC: 82442-134 | Form: TABLET, CHEWABLE
Manufacturer: Target corporation
Category: otc | Type: Human OTC Drug Label
Date: 20240613

ACTIVE INGREDIENTS: DIMETHICONE 125 mg/1 1
INACTIVE INGREDIENTS: D&C RED NO. 30 ALUMINUM LAKE; MAGNESIUM STEARATE; CELLULOSE, MICROCRYSTALLINE; SORBITOL; SUCROSE; MALTODEXTRIN; DEXTROSE, UNSPECIFIED FORM

up and up Extra strength Gas Relief Cherry 134

ACTIVE INGREDIENT(in each tablet)

Simethicone 125 mg

PURPOSE

Anti-gas

USE(S)

relieves:

- pressure
- bloating
- symptoms referred to as gas

WARNINGS

.

KEEP OUT OF REACH OF CHILDREN.

In case of overdose, get medical help or contact a poison control center immediately.

DIRECTIONS

- chew 1 to 2 tablets thoroughly as needed after meals and at bedtime
- do not exceed 4 tablets in a 24 hour period except under the advice and supervision of a physician.

OTHER INFORMATION

- do not use if any individual blister unit is broken or open
- store at room temperature
- avoid high humidity and excessive heat, above 40ºC (104ºF)

INACTIVE INGREDIENTS

D&C red # 30 aluminum lake, dextrose, flavor, magnesium stearate, maltodextrin, microcrystalline cellulose, sorbitol, sucrose.

PRINCIPAL DISPLAY PANEL

up&up

Extra strength Gas Relief

Simethicone, 125 mg Chewable Tablets

Compare to active ingredient in Gas-X®E-X*

NDC82442-134-34

Extra Strength Gas Relief

Simethicone, 125 mg Chewable Tablets

Provides fast relief from gas pressure, bloating and discomfort

cherry Flavor

up&up

Actual Size

48 Tablets

48 CHEWABLE TABLETS